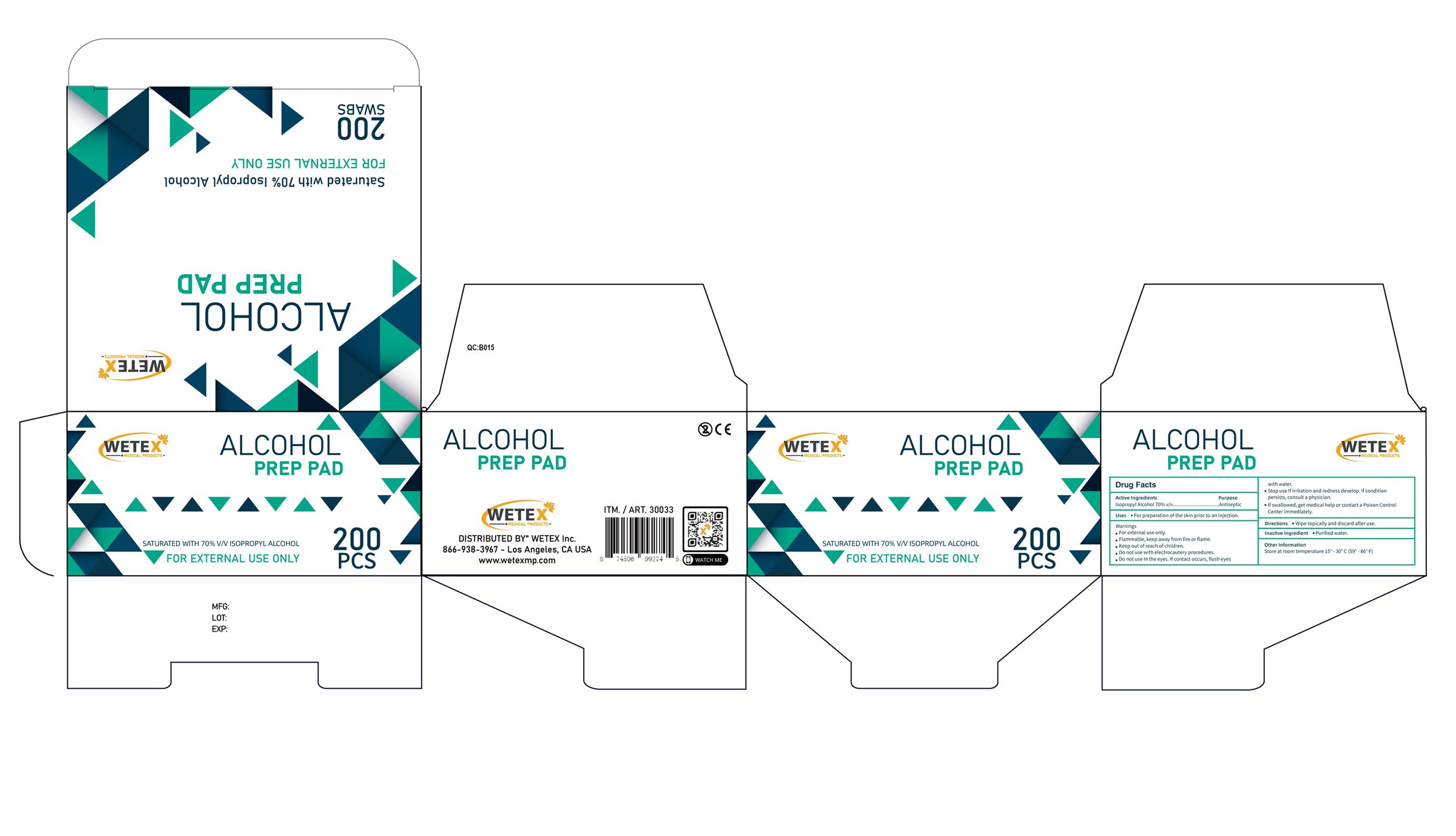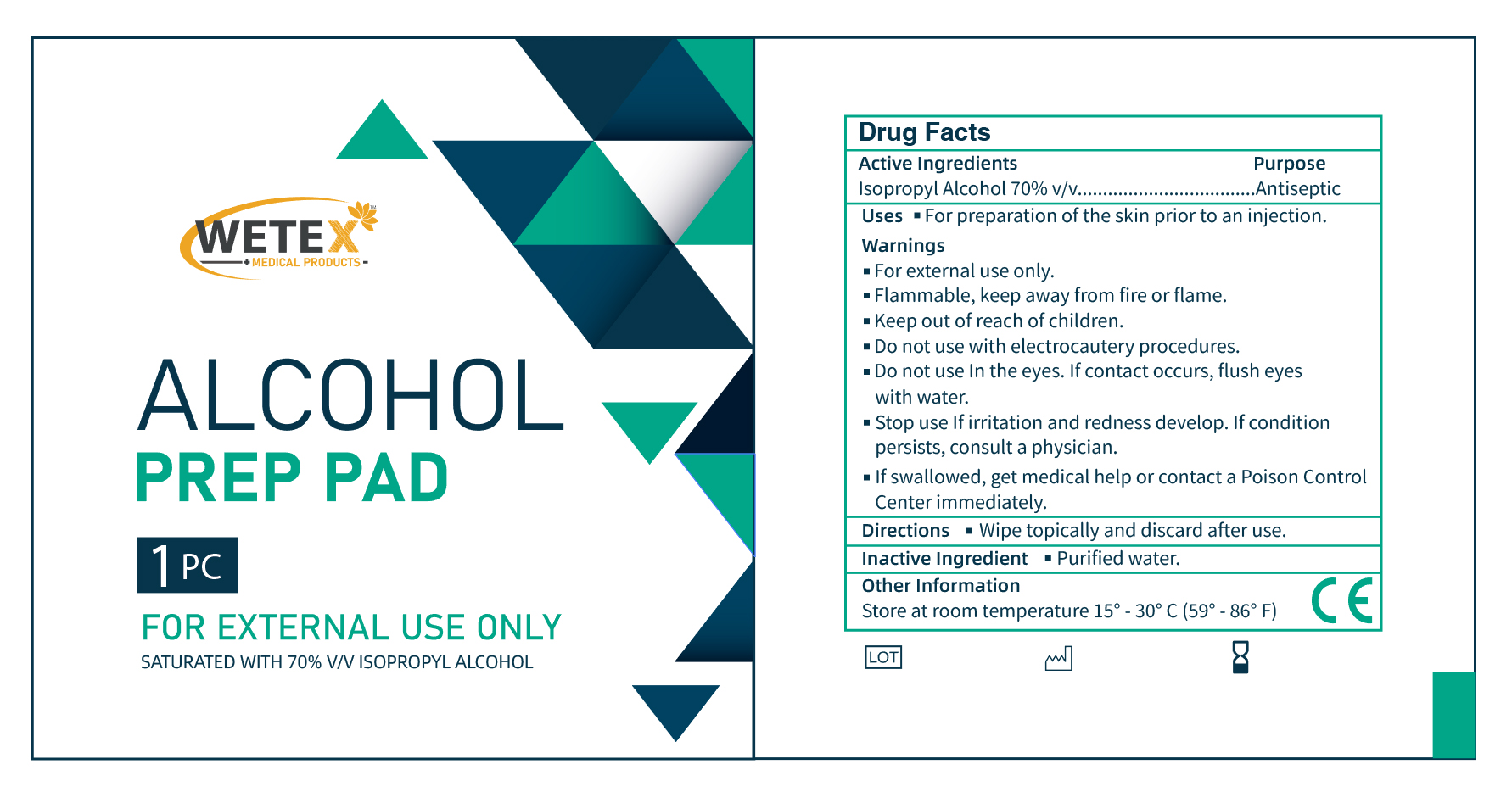 DRUG LABEL: Wetex Alcohol Prep Pad
NDC: 82826-001 | Form: CLOTH
Manufacturer: Wetex Inc
Category: otc | Type: HUMAN OTC DRUG LABEL
Date: 20220705

ACTIVE INGREDIENTS: ISOPROPYL ALCOHOL 70 mL/100 mL
INACTIVE INGREDIENTS: WATER

Wetex Alcohol Prep Pad

Active Ingredients

Isopropyl Alcohol 70%......................Antiseptic

Purpose

Antiseptic

Uses

For preparation of the skin prior to an injection

Warnings

- For external use only.
- Flammable, keep away from fire or flame.

- Do not use with electrocautery procedures.
- Do not use in the eyes. If contact occurs, flush eyes with water.

Stop use

- Stop use if irritation and redness develop.If condition persists consult your health care parctitioner.

- Keep out of reach of children.
- If swallowed, get medical help or contact a Poison Control Center right away

Directions

Wipe topically and discard after use.

Other information

Store at room temperature 15ºC - 30ºC (59ºF-86ºF)

Inactive Ingredient

Purified Water

PACKAGE LABEL

82826-001-01 Inner

WETEX

MEDICAL PRODUCTS

ALCOHOL PREP PAD

1 PC

FOR EXTERNAL USE ONLY

SATURED WITH 70% V/V ISOPROPYL ALCOHOL

82826-001-01 Outer

WETEX

MEDICAL PRODUCTS

ALCOHOL PREP PAD

SATURED WITH 70% V/V ISOPROPYL ALCOHOL

FOR EXTERNAL USE ONLY

200 PCS